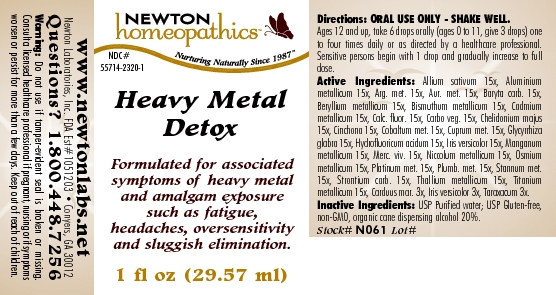 DRUG LABEL: Heavy Metal Detox   
NDC: 55714-2320 | Form: LIQUID
Manufacturer: Newton Laboratories, Inc.
Category: homeopathic | Type: HUMAN OTC DRUG LABEL
Date: 20110301

ACTIVE INGREDIENTS: Garlic 15 [hp_X]/1 mL; Aluminum 15 [hp_X]/1 mL; Silver 15 [hp_X]/1 mL; Gold 15 [hp_X]/1 mL; Barium Carbonate 15 [hp_X]/1 mL; Beryllium 15 [hp_X]/1 mL; Bismuth 15 [hp_X]/1 mL; Cadmium 15 [hp_X]/1 mL; Calcium Fluoride 15 [hp_X]/1 mL; Activated Charcoal 15 [hp_X]/1 mL; Chelidonium Majus 15 [hp_X]/1 mL; Cinchona Officinalis Bark 15 [hp_X]/1 mL; Cobalt 15 [hp_X]/1 mL; Copper 15 [hp_X]/1 mL; Glycyrrhiza Glabra 15 [hp_X]/1 mL; Hydrofluoric Acid 15 [hp_X]/1 mL; Iris Versicolor Root 15 [hp_X]/1 mL; Manganese 15 [hp_X]/1 mL; Mercury 15 [hp_X]/1 mL; Nickel 15 [hp_X]/1 mL; Osmium 15 [hp_X]/1 mL; Platinum 15 [hp_X]/1 mL; Lead 15 [hp_X]/1 mL; Tin 15 [hp_X]/1 mL; Strontium Carbonate 15 [hp_X]/1 mL; Thallium 15 [hp_X]/1 mL; Titanium 15 [hp_X]/1 mL; Silybum Marianum Seed 3 [hp_X]/1 mL; Taraxacum Officinale 3 [hp_X]/1 mL
INACTIVE INGREDIENTS: Alcohol

Heavy Metal Detox

INDICATIONS & USAGE SECTION

Heavy Metal Detox Formulated for associated symptoms of heavy metal and amalgam exposure such as fatigue, headaches, oversensitivity and sluggish elimination.

DOSAGE & ADMINISTRATION SECTION

Directions: ORAL USE ONLY - SHAKE WELL. Ages 12 and up, take 6 drops orally (ages 0 to 11, give 3 drops) one to four times daily or as directed by a healthcare professional. Sensitive persons begin with 1 drop and gradually increase to full dose.

OTC - ACTIVE INGREDIENT SECTION

Allium sativum 15x, Aluminium metallicum 15x, Arg. met. 15x, Aur. met. 15x, Baryta carb. 15x, Beryllium metallicum 15x, Bismuthum metallicum 15x, Cadmium metallicum 15x, Calc. fluor. 15x, Carbo veg. 15x, Chelidonium majus 15x, Cinchona 15x, Cobaltum met. 15x, Cuprum met. 15x, Glycyrrhiza glabra 15x, Hydrofluoricum acidum 15x, Iris versicolor 15x, Manganum metallicum 15x, Merc. viv. 15x, Niccolum metallicum 15x, Osmium metallicum 15x, Platinum met. 15x, Plumb. met. 15x, Stannum met.15x, Strontium carb. 15x, Thallium metallicum 15x, Titanium metallicum 15x, Carduus mar. 3x, Iris versicolor 3x, Taraxacum 3x.

OTC - PURPOSE SECTION

Formulated for associated symptoms of heavy metal and amalgam exposure such as fatigue, headaches, oversensitivity and sluggish elimination.

INACTIVE INGREDIENT SECTION

Inactive Ingredients: USP Purified Water; USP Gluten-free, non-GMO, organic cane dispensing alcohol 20%.

QUESTIONS SECTION

www.newtonlabs.net Newton Laboratories, Inc. FDA Est # 1051203 - Conyers, GA 30012
Questions? 1.800.448.7256

WARNINGS SECTION

Warning: Do not use if tamper - evident seal is broken or missing. Consult a licensed healthcare professional if pregnant, nursing or if symptoms worsen or persist for more than a few days. Keep out of reach of children.

OTC - PREGNANCY OR BREAST FEEDING SECTION

Consult a licensed healthcare professional if pregnant, nursing or if symptoms worsen or persist for more than a few days.

OTC - KEEP OUT OF REACH OF CHILDREN SECTION

Keep out of reach of children.